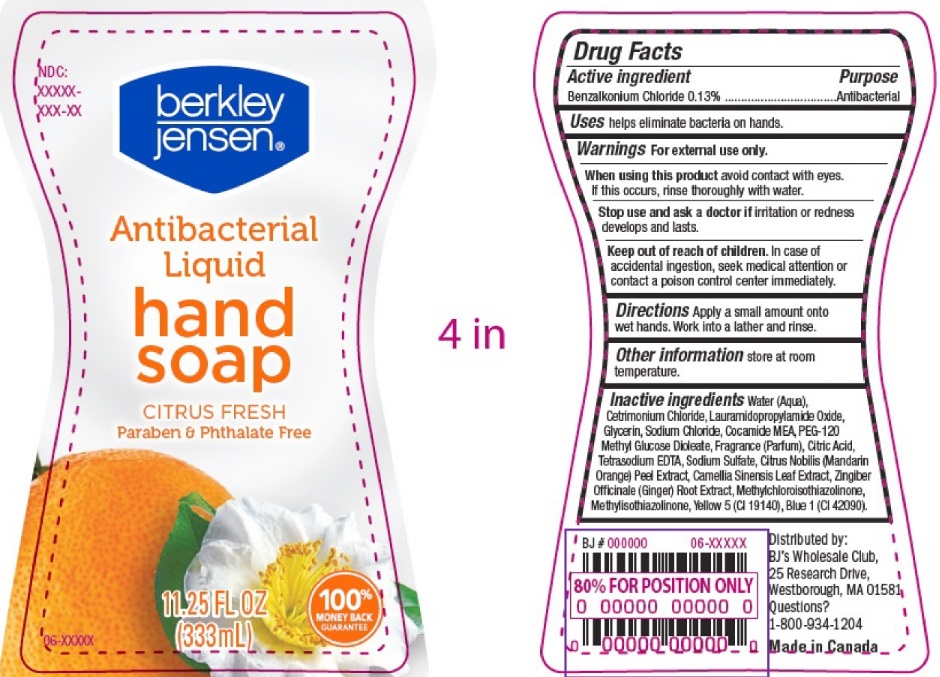 DRUG LABEL: berkley jensen
NDC: 63148-400 | Form: SOAP
Manufacturer: Apollo Health and Beauty Care
Category: otc | Type: HUMAN OTC DRUG LABEL
Date: 20241020

ACTIVE INGREDIENTS: BENZALKONIUM CHLORIDE 130 mg/100 mL
INACTIVE INGREDIENTS: GREEN TEA LEAF; SODIUM SULFATE; GLYCERIN; CETRIMONIUM CHLORIDE; SODIUM CHLORIDE; LAURAMIDOPROPYLAMINE OXIDE; METHYLCHLOROISOTHIAZOLINONE; WATER; METHYLISOTHIAZOLINONE; PEG-120 METHYL GLUCOSE DIOLEATE; FRAGRANCE CLEAN ORC0600327; CITRIC ACID MONOHYDRATE; EDETATE SODIUM; COCO MONOETHANOLAMIDE; BASIC YELLOW 5; FD&C BLUE NO. 1; CITRUS NOBILIS; GINGER

Berkley Jensen Citrus Fresh Antibacterial Liq Hand Soap, 63148-400-11

Active Ingredient.

Benzalkonium Chloride (0.13%)

Purpose

Antibacterial

Uses

Helps eliminate bacteria on hands.

Warnings

For external use only

When using this product

Avoid contact with eyes. If this occurs, rinse thoroughly with water.

Stop use and ask a doctor if

irritation or redness develops and lasts

Keep out of reach of children.

In case of accidental ingestion, seek medical attention or contact a poison control center immediately.

Directions

- Apply a small amount onto wet hands
- Work into a lather and rinse

Other Information

Store at room temperature

Inactive Ingredients

Water (Aqua), Cetrimonium Chloride, Lauramidopropylamide Oxide, Glycerin, Sodium Chloride, Cocamide MEA, PEG – 120 Methyl Glucose Dioleate, Fragrance (Parfum), Citric Acid, Tetrasodium EDTA, Sodium Sulfate, Citrus Nobillis (Mandarin Orange) Peel Extract, Camellia Sinensis Leaf Extract, Zingiber Officinale (Ginger) Root Extract. Methylchloroisothiazolinone, Methylisothiazolinone, Yellow 5 (CI 19140), Blue 1 (Cl 42090),